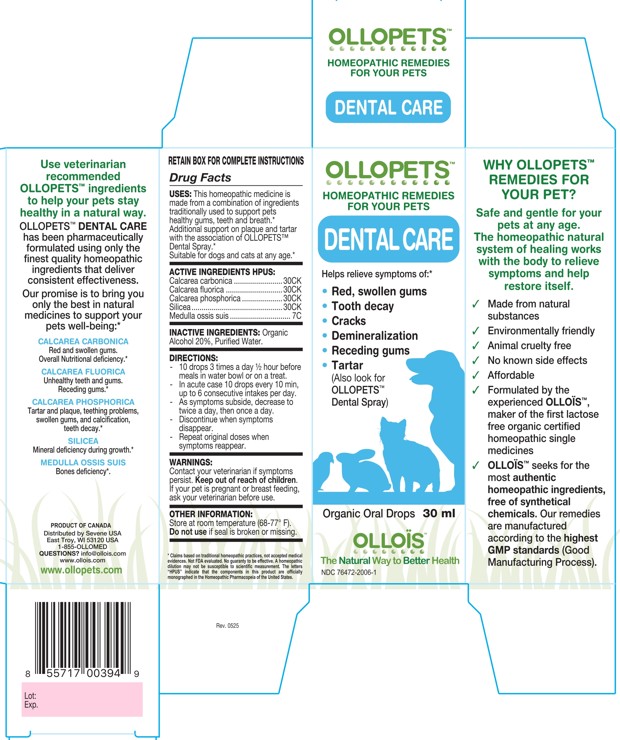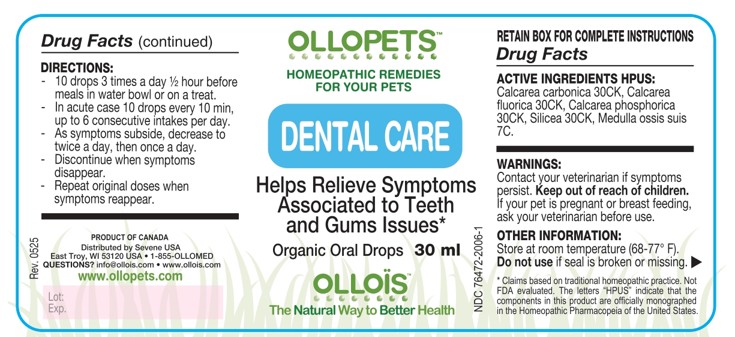 DRUG LABEL: OLLOPETS DENTAL CARE
NDC: 76472-2006 | Form: SOLUTION
Manufacturer: SEVENE USA
Category: homeopathic | Type: OTC ANIMAL DRUG LABEL
Date: 20260218

ACTIVE INGREDIENTS: OYSTER SHELL CALCIUM CARBONATE, CRUDE 30 [hp_C]/100 mL; CALCIUM FLUORIDE 30 [hp_C]/100 mL; TRIBASIC CALCIUM PHOSPHATE 30 [hp_C]/100 mL; SILICON DIOXIDE 30 [hp_C]/100 mL; SUS SCROFA BONE MARROW 7 [hp_C]/100 mL; ALCOHOL 12 [hp_X]/100 mL; WATER 12 [hp_X]/100 mL

SEVENE - OLLOPETS - DENTAL CARE

ACTIVE INGREDIENT HPUS

Calcarea carbonica ........................30CK
Calcarea fluorica ............................30CK
Calcarea phosphorica ....................30CK
Silicea .............................................30CK
Medulla ossis suis .............................. 7C